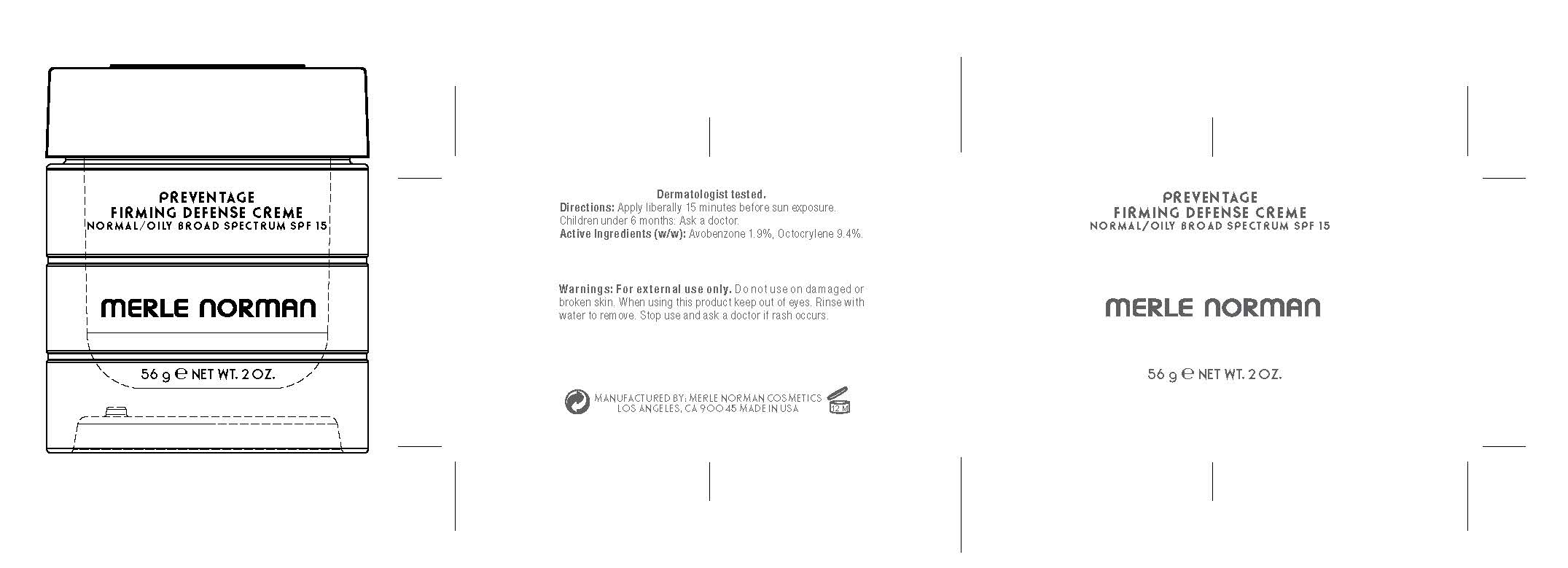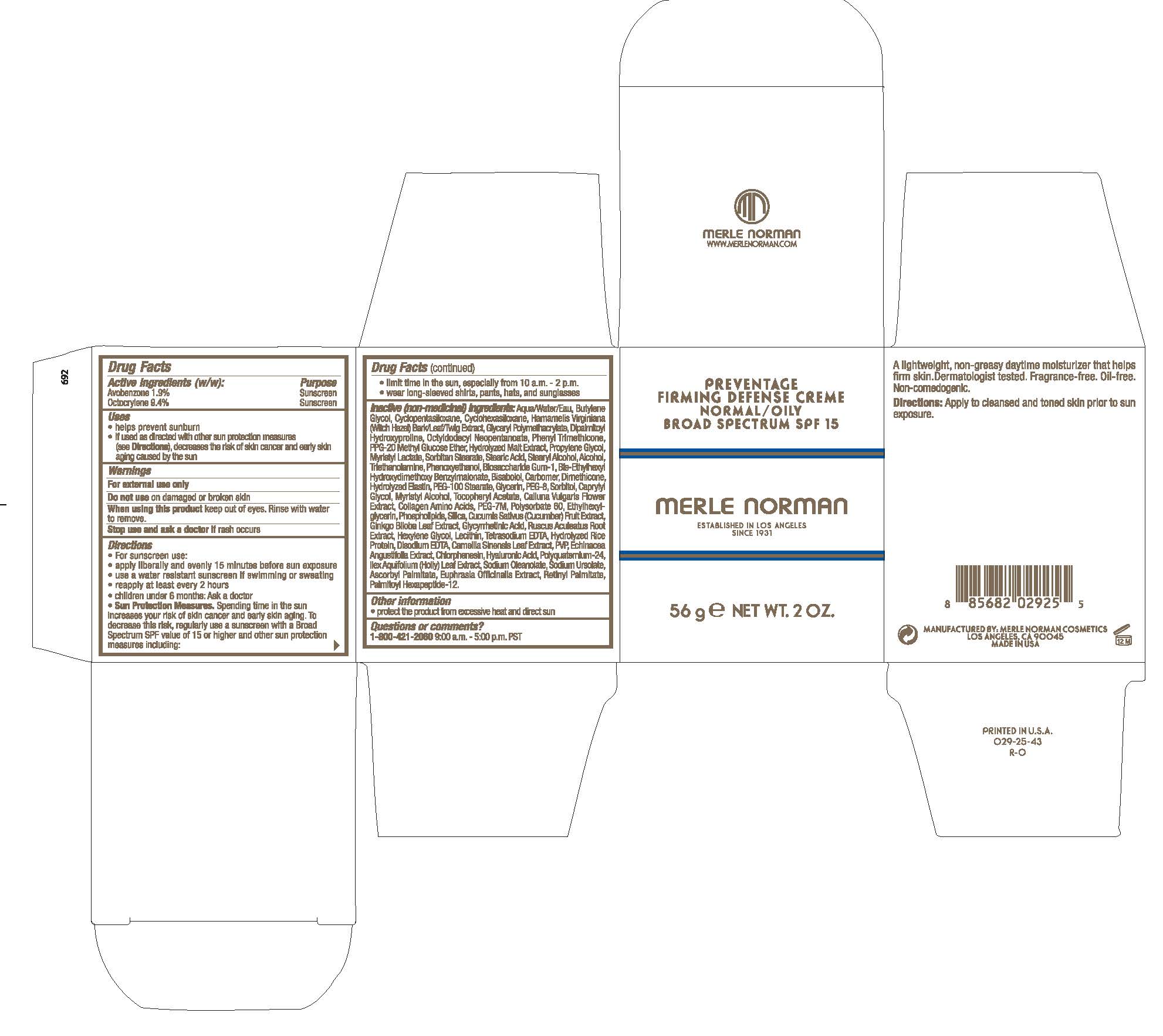 DRUG LABEL: Preventage Firming Defense Creme Normal/ Oily Broad Spectrum SPF 15
NDC: 57627-186 | Form: CREAM
Manufacturer: Merle Norman Cosmetics, Inc
Category: otc | Type: HUMAN OTC DRUG LABEL
Date: 20251119

ACTIVE INGREDIENTS: AVOBENZONE 1.9 g/100 g; OCTOCRYLENE 9.4 g/100 g
INACTIVE INGREDIENTS: POLYETHYLENE GLYCOL 400; SORBITOL; CAPRYLYL GLYCOL; MYRISTYL ALCOHOL; CALLUNA VULGARIS FLOWERING TOP; POLYETHYLENE OXIDE 300000; EDETATE DISODIUM; LECITHIN, SOYBEAN; ILEX AQUIFOLIUM LEAF; ASCORBYL PALMITATE; EUPHRASIA STRICTA; VITAMIN A PALMITATE; TROLAMINE; .ALPHA.-TOCOPHEROL ACETATE; POLYSORBATE 60; STEARYL ALCOHOL; ALCOHOL; LEVOMENOL; OCTYLDODECYL NEOPENTANOATE; PEG-100 STEARATE; OMEGA-3 FATTY ACIDS; SODIUM URSOLATE; CYCLOMETHICONE 6; HAMAMELIS VIRGINIANA TOP; PROPYLENE GLYCOL; BUTYLENE GLYCOL; PPG-20 METHYL GLUCOSE ETHER; MYRISTYL LACTATE; BIOSACCHARIDE GUM-1; DIMETHICONE; PHENYL TRIMETHICONE; SORBITAN MONOSTEARATE; GLYCERIN; STEARIC ACID; HYDROLYZED BOVINE ELASTIN (BASE; 1000 MW); CARBOMER HOMOPOLYMER, UNSPECIFIED TYPE; HEXYLENE GLYCOL; WATER; SILICON DIOXIDE; GINKGO; ENOXOLONE; GREEN TEA LEAF; RUSCUS ACULEATUS ROOT; POVIDONE; ECHINACEA ANGUSTIFOLIA WHOLE; CHLORPHENESIN; HYALURONIC ACID; EDETATE SODIUM; CUCUMBER; PALMITOYL HEXAPEPTIDE-12; CYCLOMETHICONE 5; DIPALMITOYL HYDROXYPROLINE; ETHYLHEXYLGLYCERIN; PHENOXYETHANOL

Preventage Firming Defense Creme Normal/ Oily Broad Spectrum SPF 15

Active Ingredients (w/w): Purpose

Avobenzone 1.9% Sunscreen

Octocrylene 9.4% Sunscreen

Uses

- helps prevent sunburn
- If used as directed with other sun protection measures (see Directions), decreases the risk of skin cancer and early skin aging caused by the sun.

When using this product, keep out of eyes. Rinse with water to remove.

Stop use and ask a doctor if rash occurs

Warnings

For external use only

Do not use on damaged or broken skin

Directions

- For sunscreen use:
- apply liberally and evenly 15 minutes before sun exposure
- use a water resistant sunscreen if swimming or sweating
- reapply at least every 2 hours
- children under 6 months: Ask a doctor
- Sun Protection Measures. Spending time in the sun increases your risk of skin cancer and early skin aging. To decrease this risk, regularly use a sunscreen with a Broad Spectrum SPF value of 15 or higher and other sun protection measures including:
- limit time in the sun, especially from 10 a.m. - 2 p.m.
- wear long-sleeved shirts, pants, hats, and sunglasses

INACTIVE INGREDIENT

Inactive (non-medicinal) ingredients: Aqua/Water/Eau, Butylene Glycol, Cyclopentasiloxane, Cyclohexasiloxane, Hamamelis Virginiana (Witch Hazel) Bark/leaf/twig Extract, Glyceryl Polymethacrylate, Dipalmitoyl hydroxyproline, octyldodecyl Neopentanoate, Phenyl Trimethicone, PPG-20 Methyl Glucose Ether, Hydrolyzed Malt Extract, Propylene Glycol, Myristyl Lactate, Sorbitan Stearate, Stearic Acid, Stearyl Alcohol, Alcohol, Triethanolamine, Phenoxyethanol, Biosaccharide Gum-1, Bis-Ethylhexyl Hydroxydimethoxy Benzylmalonate, Bisabolol, Carbomer, Dimethicone, Hydrolyzed Elastin, PEG-100 Stearate, Glycerin, PEG-8, Sorbitol, Caprylyl Glycol, Myristyl Alcohol, Tocopheryl Acetate, Calluna Vulgaris Flower Extract, Collagen Amino Acids, PEG-7M, Polysorbate 60, Ethylhexylglycerin, Phospholipids, Silica, Cucumis Sativus (Cucumber) Fruit Extract, Ginkgo Biloba Leaf Extract, Glycyrrhetinic Acid, Ruscus Aculeatus Root Extract, Hexylene Glycol, Lectithin, Tetrasodium EDTA, Hydrolyzed Rice Protein, Disodium EDTA, Camellia Sinensis Leaf Extract, PVP, Echinacea Angustifolia Extract, Chlorphenesin, Hyaluronic Acid, Polyquaternium-24, Ilex Aquifolium (Holly) Leaf Extract, Sodium Oleanolate, Sodium Ursolate, Ascorbyl Palmitate, Euphrasia Officinalis Extract, Retinyl Palmitate, Palmitoyl Hexapeptide-12.

PACKAGE LABEL

Preventage Firming Defense Creme

Normal / Oily

Broad Spectrum SPF 15

Merle Norman

Established in Los Angeles Since 1931

56 g Net Wt. 2 OZ